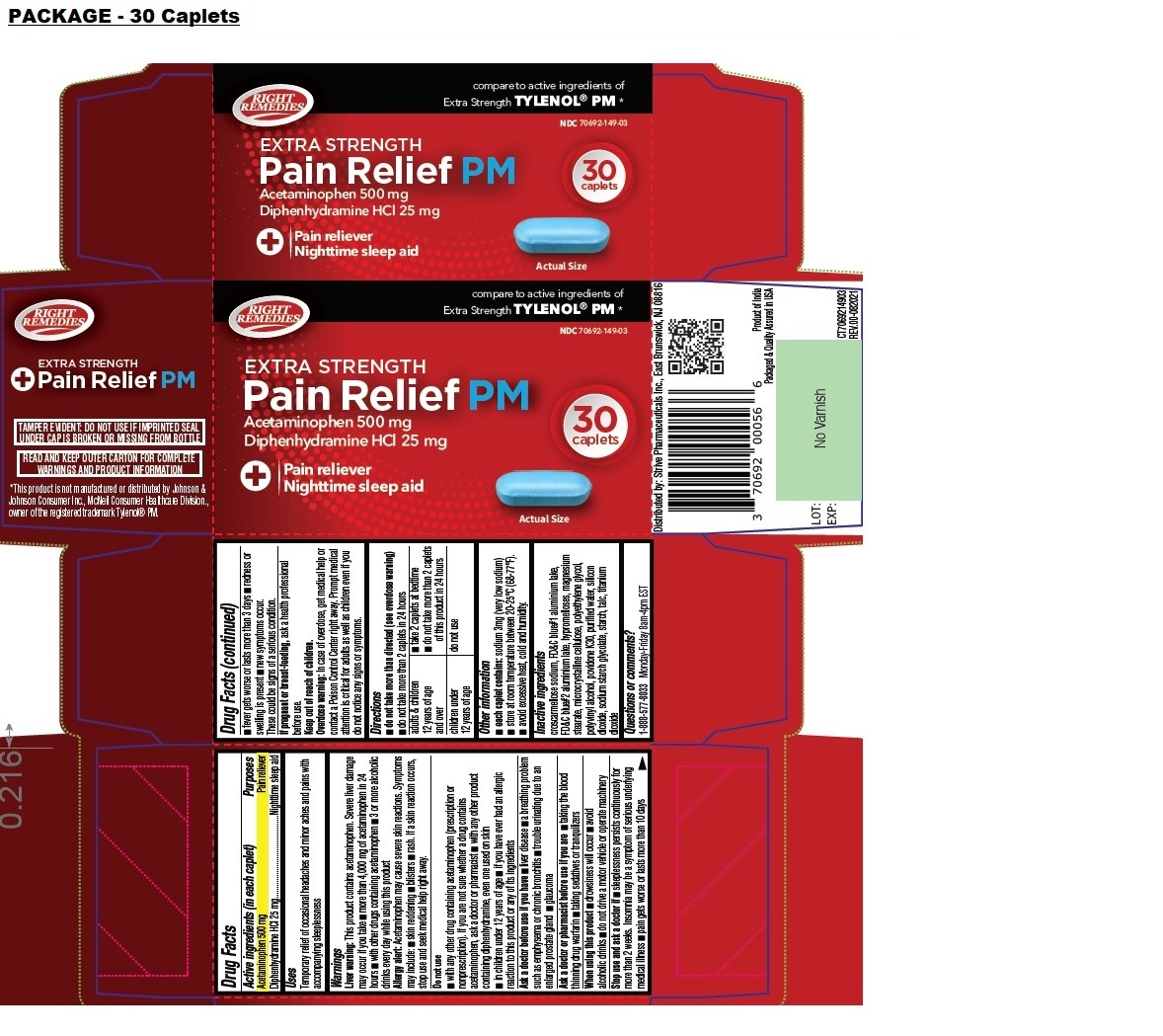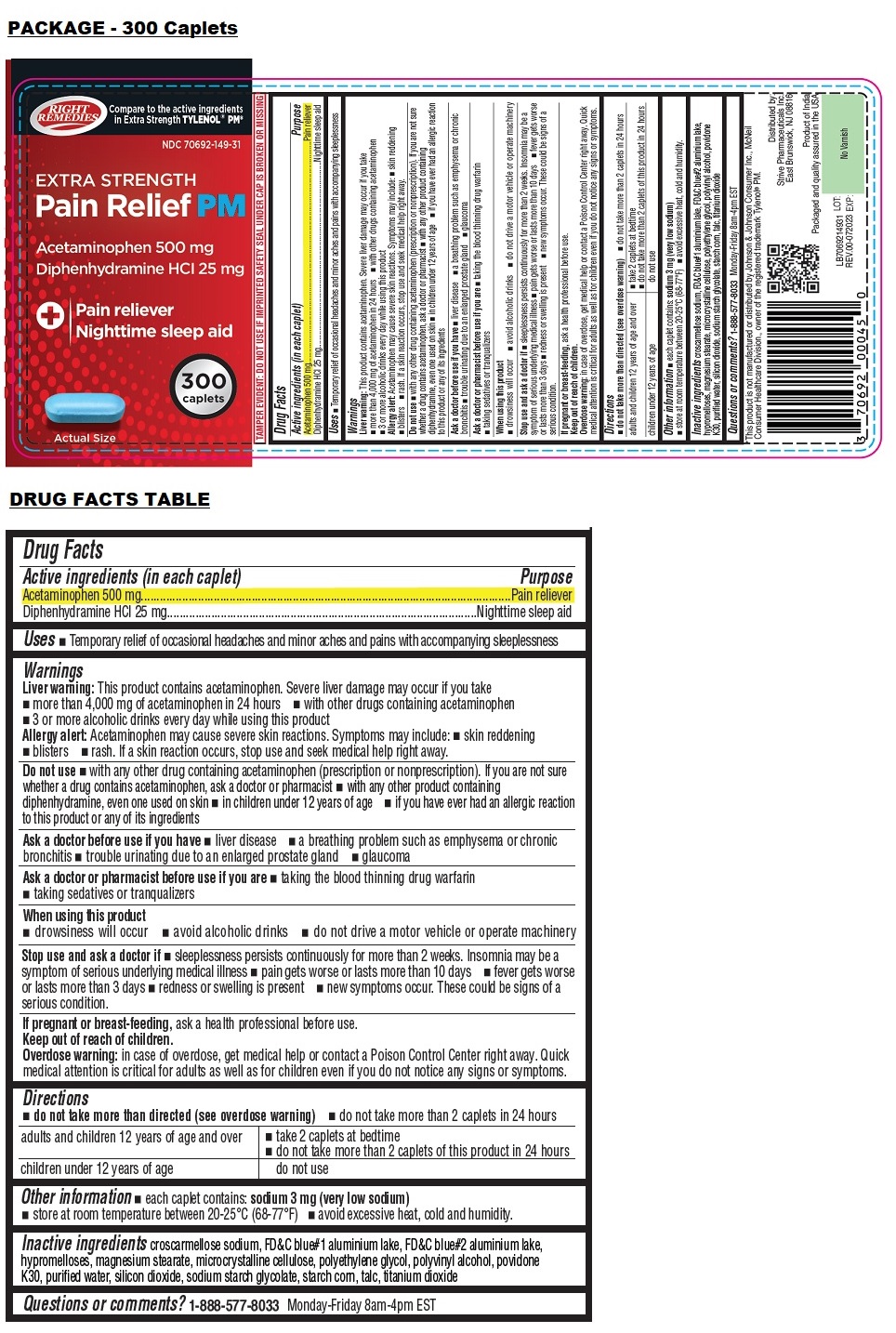 DRUG LABEL: RIGHT REMEDIES EXTRA STRENGTH PM Pain Relief
NDC: 70692-149 | Form: TABLET, FILM COATED
Manufacturer: Strive Pharmaceuticals Inc.
Category: otc | Type: HUMAN OTC DRUG LABEL
Date: 20231113

ACTIVE INGREDIENTS: ACETAMINOPHEN 500 mg/1 1; DIPHENHYDRAMINE HYDROCHLORIDE 25 mg/1 1
INACTIVE INGREDIENTS: CROSCARMELLOSE SODIUM; FD&C BLUE NO. 1 ALUMINUM LAKE; FD&C BLUE NO. 2; HYPROMELLOSE, UNSPECIFIED; MAGNESIUM STEARATE; MICROCRYSTALLINE CELLULOSE; POLYETHYLENE GLYCOL, UNSPECIFIED; POLYVINYL ALCOHOL, UNSPECIFIED; POVIDONE K30; WATER; SILICON DIOXIDE; SODIUM STARCH GLYCOLATE TYPE A; STARCH, CORN; TALC; TITANIUM DIOXIDE

RIGHT REMEDIES EXTRA STRENGTH Pain Relief PM

Active ingredients (in each caplet)

Acetaminophen 500 mg
Diphenhydramine HCl 25 mg

Purposes

Pain reliever
Nighttime sleep aid

Uses

Temporary relief of occasional headaches and minor aches and pains with accompanying sleeplessness

Warnings

Liver warning: This product contains acetaminophen. Severe liver damage may occur if you take • more than 4,000 mg of acetaminophen in 24 hours • with other drugs containing acetaminophen • 3 or more alcoholic drinks every day while using this product

Allergy alert: Acetaminophen may cause severe skin reactions. Symptoms may include: • skin reddening • blisters • rash. If a skin reaction occurs, stop use and seek medical help right away.

Do not use
• with any other drug containing acetaminophen (prescription or nonprescription). If you are not sure whether a drug contains acetaminophen, ask a doctor or pharmacist • with any other product containing diphenhydramine, even one used on skin
• in children under 12 years of age • if you have ever had an allergic reaction to this product or any of its ingredients

Ask a doctor before use if you have • liver disease • a breathing problem such as emphysema or chronic bronchitis • trouble urinating due to an enlarged prostate gland • glaucoma

Ask a doctor or a pharmacist before use if you are • taking the blood thinning drug warfarin • taking sedatives or tranquilizers

When using this product • drowsiness will occur • avoid alcoholic drinks • do not drive a motor vehicle or operate machinery

Stop use and ask a doctor if • sleeplessness persists continuously for more than 2 weeks. Insomnia may be a symptom of serious underlying medical illness • pain gets worse or lasts more than 10 days • fever gets worse or lasts more than 3 days • redness or swelling is present • new symptoms occur.
These could be signs of a serious condition

If pregnant or breast-feeding, ask a health professional before use.

Keep out of reach of children.
Overdose warning: In case of overdose, get medical help or contact a Poison Control Center right away. Prompt medical attention is critical for adults as well as children even if you do not notice any signs or symptoms.

Directions

• do not take more than directed (see overdose warning)
• do not take more than 2 caplets in 24 hours

adults & children 12 years of age and over | • take 2 caplets at bedtime • do not take more than 2 caplets of this product in 24 hours
children under 12 years of age | do not use

Other information

• each caplet contains: sodium 3 mg (very low sodium)
• store at room temperature between 20-25ºC (68-77ºF).
• avoid excessive heat, cold and humidity.

Inactive ingredients

croscarmellose sodium, FD&C blue#1 aluminium lake, FD&C blue#2 aluminium lake, hypromelloses, magnesium stearate, microcrystalline cellulose, polyethylene glycol, polyvinyl alcohol, povidone K30, purified water, silicon dioxide, sodium starch glycolate, starch, talc, titanium dioxide

Questions or comments?

1-888-577-8033 Monday-Friday 8am-4pm EST

compare to active ingredients of Extra Strength TYLENOL® PM*

TAMPER EVIDENT: DO NOT USE IF IMPRINTED SEAL UNDER CAP IS BROKEN OR MISSING FROM BOTTLE

READ AND KEEP OUTER CARTON FOR COMPLETE WARNINGS AND PRODUCT INFORMATION

*This product is not manufactured or distributed by Johnson & Johnson Consumer Inc., McNeil Consumer Healthcare Division., owner of the registered trademark Tylenol® PM.

Distributed by: Strive Pharmaceuticals Inc., East Brunswick, NJ 08816

Product of India

Packaged & Quality Assured in USA

CT7069214903
REV.00-082021